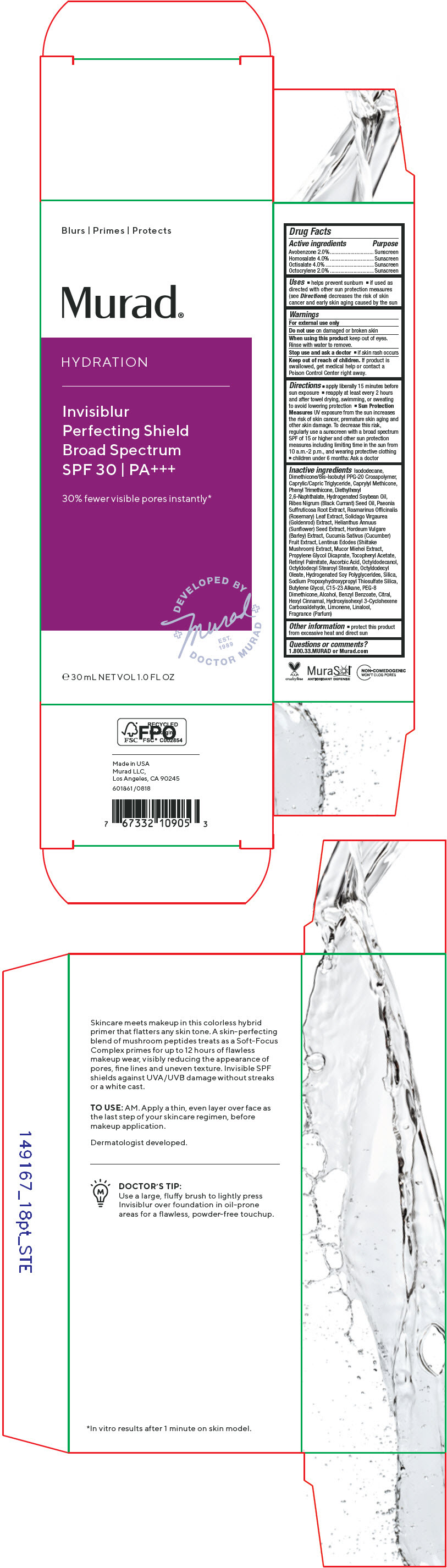 DRUG LABEL: Hydration Invisiblur Perfecting Shield Broad Spectrum 
NDC: 70381-118 | Form: CREAM
Manufacturer: Murad, LLC
Category: otc | Type: HUMAN OTC DRUG LABEL
Date: 20210709

ACTIVE INGREDIENTS: AVOBENZONE 2 g/100 mL; HOMOSALATE 4 g/100 mL; OCTISALATE 4 g/100 mL; OCTOCRYLENE 2 g/100 mL
INACTIVE INGREDIENTS: ISODODECANE; DIMETHICONE/BIS-ISOBUTYL PPG-20 CROSSPOLYMER; MEDIUM-CHAIN TRIGLYCERIDES; CAPRYLYL TRISILOXANE; PHENYL TRIMETHICONE; DIETHYLHEXYL 2,6-NAPHTHALATE; HYDROGENATED SOYBEAN OIL; RIBES NIGRUM SEED OIL; PAEONIA X SUFFRUTICOSA ROOT; ROSEMARY; SUNFLOWER SEED; CUCUMBER; PROPYLENE GLYCOL DICAPRATE; .ALPHA.-TOCOPHEROL ACETATE; VITAMIN A PALMITATE; ASCORBIC ACID; OCTYLDODECANOL; OCTYLDODECYL STEAROYL STEARATE; OCTYLDODECYL OLEATE; SILICON DIOXIDE; SODIUM PROPOXYHYDROXYPROPYL THIOSULFATE SILICA; BUTYLENE GLYCOL; C15-23 ALKANE; PEG-8 DIMETHICONE; ALCOHOL; BENZYL BENZOATE; .ALPHA.-HEXYLCINNAMALDEHYDE; LIMONENE, (+)-; LINALOOL, (+/-)-; SOLIDAGO VIRGAUREA FLOWERING TOP; SHIITAKE MUSHROOM; MUCOR PLUMBEUS; HYDROGENATED SOYBEAN LECITHIN; HORDEUM VULGARE WHOLE

Hydration Invisiblur Perfecting Shield Broad Spectrum SPF 30

Drug Facts

ACTIVE INGREDIENT

Active ingredients | Purpose
Avobenzone 2.0% | Sunscreen
Homosalate 4.0% | Sunscreen
Octisalate 4.0% | Sunscreen
Octocrylene 2.0% | Sunscreen

Uses

- helps prevent sunburn
- if used as directed with other sun protection measures (see Directions) decreases the risk of skin cancer and early skin aging caused by the sun

Warnings

For external use only

Do not use on damaged or broken skin

When using this product keep out of eyes. Rinse with water to remove.

Stop use and ask a doctor

- if skin rash occurs

Keep out of reach of children. If product is swallowed, get medical help or contact a Poison Control Center right away.

Directions

- apply liberally 15 minutes before sun exposure
- reapply at least every 2 hours and after towel drying, swimming, or sweating to avoid lowering protection
- Sun Protection Measures UV exposure from the sun increases the risk of skin cancer, premature skin aging and other skin damage. To decrease this risk, regularly use a sunscreen with a broad spectrum SPF of 15 or higher and other sun protection measures including limiting time in the sun from 10 a.m.-2 p.m., and wearing protective clothing
- children under 6 months: Ask a doctor

Inactive ingredients

Isododecane, Dimethicone/Bis-Isobutyl PPG-20 Crosspolymer, Caprylic/Capric Triglyceride, Caprylyl Methicone, Phenyl Trimethicone, Diethylhexyl 2,6-Naphthalate, Hydrogenated Soybean Oil, Ribes Nigrum (Black Currant) Seed Oil, Paeonia Suffruticosa Root Extract, Rosmarinus Ofﬁcinalis (Rosemary) Leaf Extract, Solidago Virgaurea (Goldenrod) Extract, Helianthus Annuus (Sunﬂower) Seed Extract, Hordeum Vulgare (Barley) Extract, Cucumis Sativus (Cucumber) Fruit Extract, Lentinus Edodes (Shiitake Mushroom) Extract, Mucor Miehei Extract, Propylene Glycol Dicaprate, Tocopheryl Acetate, Retinyl Palmitate, Ascorbic Acid, Octyldodecanol, Octyldodecyl Stearoyl Stearate, Octyldodecyl Oleate, Hydrogenated Soy Polyglycerides, Silica, Sodium Propoxyhydroxypropyl Thiosulfate Silica, Butylene Glycol, C15-23 Alkane, PEG-8 Dimethicone, Alcohol, Benzyl Benzoate, Citral, Hexyl Cinnamal, Hydroxyisohexyl 3-Cyclohexene Carboxaldehyde, Limonene, Linalool, Fragrance (Parfum)

Other information

- protect this product from excessive heat and direct sun

Questions or comments?

1.800.33.MURAD or Murad.com

PRINCIPAL DISPLAY PANEL - 30 mL Bottle Carton

Blurs | Primes | Protects

Murad®

HYDRATION

Invisiblur
Perfecting Shield
Broad Spectrum
SPF 30 | PA^+++

30% fewer visible pores instantly*

DEVELOPED BY
+Murad+
EST.
1989
DOCTOR MURAD

e 30 mL NET VOL 1.0 FL OZ